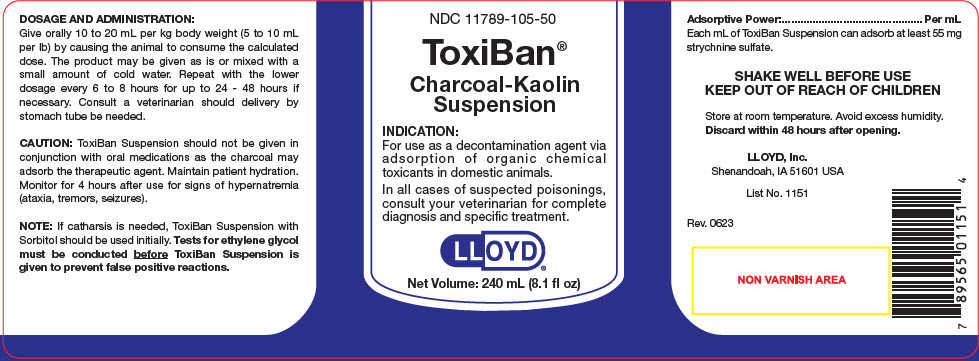 DRUG LABEL: ToxiBan
NDC: 11789-105 | Form: SUSPENSION
Manufacturer: LLOYD, Inc. of Iowa
Category: animal | Type: OTC ANIMAL DRUG LABEL
Date: 20230828

ACTIVE INGREDIENTS: ACTIVATED CHARCOAL 55 [arb'U]/1 mL
INACTIVE INGREDIENTS: SORBITOL; KAOLIN

ToxiBan®

VETERINARY INDICATIONS

INDICATION:

For use as a decontamination agent via adsorption of organic chemical toxicants in domestic animals.

In all cases of suspected poisonings, consult your veterinarian for complete diagnosis and specific treatment.

DOSAGE AND ADMINISTRATION:

Give orally 10 to 20 mL per kg body weight (5 to 10 mL per lb) by causing the animal to consume the calculated dose. The product may be given as is or mixed with a small amount of cold water. Repeat with the lower dosage every 6 to 8 hours for up to 24 - 48 hours if necessary. Consult a veterinarian should delivery by stomach tube be needed.

PRECAUTIONS

CAUTION: ToxiBan Suspension should not be given in conjunction with oral medications as the charcoal may adsorb the therapeutic agent. Maintain patient hydration. Monitor for 4 hours after use for signs of hypernatremia (ataxia, tremors, seizures).

NOTE: If catharsis is needed, ToxiBan Suspension with Sorbitol should be used initially. Tests for ethylene glycol must be conducted before ToxiBan Suspension is given to prevent false positive reactions.

Adsorptive Power:........................ Per mL

Each mL of ToxiBan Suspension can adsorb at least 55 mg strychnine sulfate.

STORAGE AND HANDLING

SHAKE WELL BEFORE USE

KEEP OUT OF REACH OF CHILDREN

Store at room temperature. Avoid excess humidity.

Discard within 48 hours after opening.

LLOYD, lnc.
Shenandoah, IA 51601 USA

List No. 1151

Rev. 0623

PRINCIPAL DISPLAY PANEL - 240 mL Bottle Label

NDC 11789-105-50

ToxiBan®

Charcoal-Kaolin
Suspension

INDICATION:

For use as a decontamination agent via
adsorption of organic chemical
toxicants in domestic animals.

In all cases of suspected poisonings,
consult your veterinarian for complete
diagnosis and specific treatment.

LLOYD®

Net Volume: 240 mL (8.1 fl oz)